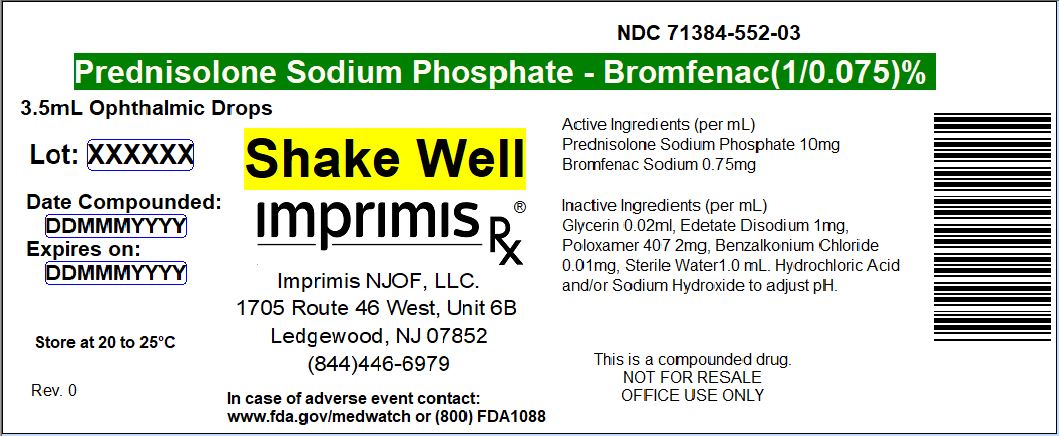 DRUG LABEL: Pred Phos - Brom
NDC: 71384-552 | Form: SOLUTION/ DROPS
Manufacturer: Imprimis NJOF, LLC
Category: prescription | Type: HUMAN PRESCRIPTION DRUG LABEL
Date: 20180608

ACTIVE INGREDIENTS: PREDNISOLONE SODIUM PHOSPHATE 10 mg/1 mL; BROMFENAC SODIUM 0.75 mg/1 mL

STORAGE AND HANDLING

Store at 20° to 25° C (68° to 77° F)